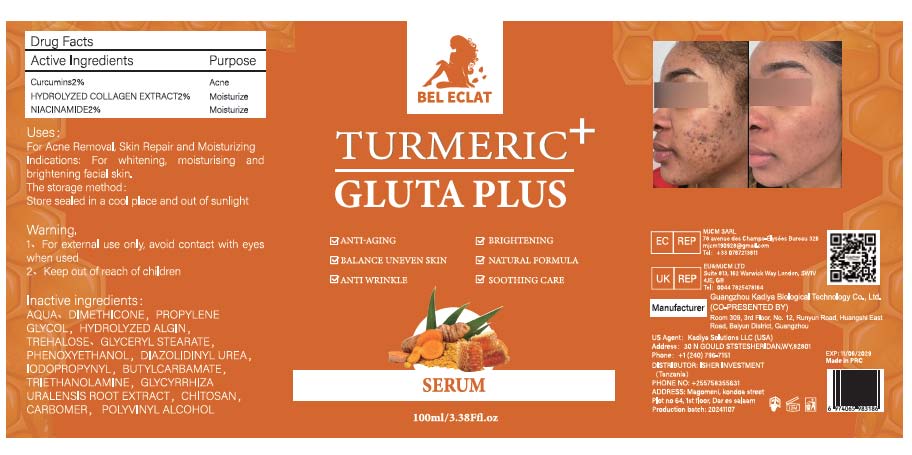 DRUG LABEL: TURMERIC SERUM
NDC: 84423-064 | Form: CREAM, AUGMENTED
Manufacturer: Guangzhou Kadiya Biotechnology Co., Ltd.
Category: otc | Type: HUMAN OTC DRUG LABEL
Date: 20241218

ACTIVE INGREDIENTS: NIACINAMIDE 2 g/100 mL
INACTIVE INGREDIENTS: IODOPROPYNYL BUTYLCARBAMATE; POLIGLUSAM; GLYCERYL STEARATE; PHENOXYETHANOL; CARBOMER; TRIETHANOLAMINE; POLYVINYL ALCOHOL; DIMETHICONE 1000; PROPYLENE GLYCOL; DIAZOLIDINYL UREA; GLYCYRRHIZA GLABRA (LICORICE) ROOT; TREHALOSE; AQUA; LAMINARIA DIGITATA HYDROLYZED ALGINIC ACID

PURPOSE

For Acne Removal, Skin Repair and Moisturizing
Indications: For whitening, moisturising and brightening facial skin.

INACTIVE INGREDIENT

AQUA、DIMETHICONE，PROPYLENE GLYCOL，HYDROLYZED ALGIN，TREHALOSE、GLYCERYL STEARATE，PHENOXYETHANOL，DIAZOLIDINYL UREA，IODOPROPYNYL，BUTYLCARBAMATE，TRIETHANOLAMINE，GLYCYRRHIZA URALENSIS ROOT EXTRACT，CHITOSAN，CARBOMER， POLYVINYL ALCOHOL

WARNINGS

1、For external use only, avoid contact with eyes when used
2、Keep out of reach of children

INDICATIONS AND USAGE

For Acne Removal, Skin Repair and Moisturizing

DOSAGE AND ADMINISTRATION

Forwhitening, moisturising andbrightening facial skin

KEEP OUT OF REACH OF CHILDREN SECTION

ACTIVE INGREDIENT

Curcumins2% Acne
HYDROLYZED COLLAGEN EXTRACT2% Moisturize
NIACINAMIDE2% Moisturize

PACKAGE LABEL

Active Ingredients
Curcumins 2%
HYDROLYZED COLLAGEN EXTRACT 2%
NIACINAMIDE 2%

Uses：
For Acne Removal, Skin Repair and Moisturizing
Indications: For whitening, moisturising and brightening facial skin.

The storage method：
Store sealed in a cool place and out of sunlight

Warning.
1、For external use only, avoid contact with eyes when used
2、Keep out of reach of children

Inactive ingredients：
AQUA、DIMETHICONE，PROPYLENE GLYCOL，HYDROLYZED ALGIN，TREHALOSE、GLYCERYL STEARATE，PHENOXYETHANOL，DIAZOLIDINYL UREA，IODOPROPYNYL，BUTYLCARBAMATE，TRIETHANOLAMINE，GLYCYRRHIZA URALENSIS ROOT EXTRACT，CHITOSAN，CARBOMER， POLYVINYL ALCOHOL